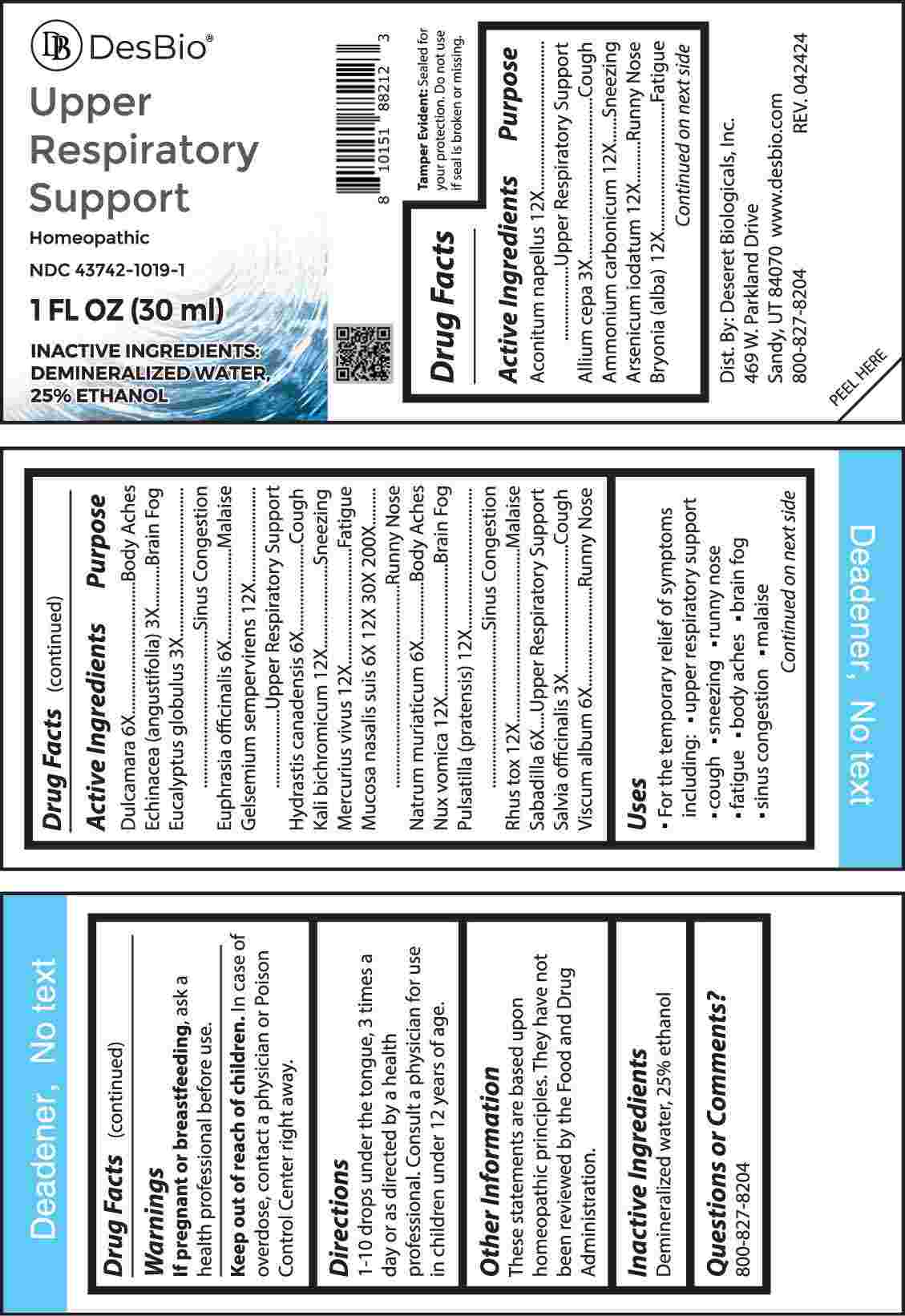 DRUG LABEL: Upper Respiratory Support
NDC: 43742-1019 | Form: LIQUID
Manufacturer: Deseret Biologicals, Inc.
Category: homeopathic | Type: HUMAN OTC DRUG LABEL
Date: 20240823

ACTIVE INGREDIENTS: ONION 3 [hp_X]/1 mL; ECHINACEA ANGUSTIFOLIA WHOLE 3 [hp_X]/1 mL; EUCALYPTUS GLOBULUS LEAF 3 [hp_X]/1 mL; SAGE 3 [hp_X]/1 mL; SOLANUM DULCAMARA TOP 6 [hp_X]/1 mL; EUPHRASIA STRICTA 6 [hp_X]/1 mL; GOLDENSEAL 6 [hp_X]/1 mL; SODIUM CHLORIDE 6 [hp_X]/1 mL; SCHOENOCAULON OFFICINALE SEED 6 [hp_X]/1 mL; VISCUM ALBUM FRUITING TOP 6 [hp_X]/1 mL; SUS SCROFA NASAL MUCOSA 6 [hp_X]/1 mL; ACONITUM NAPELLUS WHOLE 12 [hp_X]/1 mL; AMMONIUM CARBONATE 12 [hp_X]/1 mL; ARSENIC TRIOXIDE 12 [hp_X]/1 mL; BRYONIA ALBA ROOT 12 [hp_X]/1 mL; GELSEMIUM SEMPERVIRENS ROOT 12 [hp_X]/1 mL; POTASSIUM DICHROMATE 12 [hp_X]/1 mL; MERCURY 12 [hp_X]/1 mL; STRYCHNOS NUX-VOMICA SEED 12 [hp_X]/1 mL; PULSATILLA PRATENSIS WHOLE 12 [hp_X]/1 mL; TOXICODENDRON PUBESCENS LEAF 12 [hp_X]/1 mL
INACTIVE INGREDIENTS: WATER; ALCOHOL

DRUG FACTS:

ACTIVE INGREDIENTS:

Aconitum Napellus 12X, Allium Cepa 3X, Ammonium Carbonicum 12X, Arsenicum Iodatum 12X, Bryonia (Alba) 12X, Dulcamara 6X, Echinacea (Angustifolia) 3X, Eucalyptus Globulus 3X, Euphrasia Officinalis 6X, Gelsemium Sempervirens 12X, Hydrastis Canadensis 6X, Kali Bichromicum 12X, Mercurius Vivus 12X, Mucosa Nasalis Suis 6X, 12X, 30X, 200X, Natrum Muriaticum 6X, Nux Vomica 12X, Pulsatilla (Pratensis) 12X, Rhus Tox 12X, Sabadilla 6X, Salvia Officinalis 3X, Viscum Album 6X.

PURPOSE:

Aconitum Napellus – Upper Respiratory Support, Allium Cepa – Cough, Ammonium Carbonicum - Sneezing, Arsenicum Iodatum – Runny Nose, Bryonia (Alba) - Fatigue, Dulcamara – Body Aches, Echinacea (Angustifolia) – Brain Fog, Eucalyptus Globulus – Sinus Congestion, Euphrasia Officinalis - Malaise, Gelsemium Sempervirens – Upper Respiratory Support, Hydrastis Canadensis - Cough, Kali Bichromicum - Sneezing, Mercurius Vivus - Fatigue, Mucosa Nasalis Suis – Runny Nose, Natrum Muriaticum – Body Aches, Nux Vomica – Brain Fog, Pulsatilla (Pratensis) – Sinus Congestion, Rhus Tox - Malaise, Sabadilla – Upper Respiratory Support, Salvia Officinalis - Cough, Viscum Album – Runny Nose

USES:

• For the temporary relief of symptoms including:

• upper respiratory support • cough • sneezing • runny nose

• fatigue • body aches • brain fog • sinus congestion • malaise

These statements are based upon homeopathic principles. They have not been reviewed by the Food and Drug Administration.

WARNINGS:

If pregnant or breast-feeding, ask a health professional before use.

Keep out of reach of children. In case of overdose, contact a physician or Poison Control Center right away.

Tamper Evident: Sealed for your protection. Do not use if seal is broken or missing.

KEEP OUT OF REACH OF CHILDREN:

In case of overdose, contact a physician or Poison Control Center right away.

DIRECTIONS:

1-10 drops under the tongue, 3 times a day or as directed by a health professional. Consult a physician for use in children under 12 years of age.

INACTIVE INGREDIENTS:

Demineralized water, 25% ethanol

QUESTIONS:

Dist. By: Deseret Biologicals, Inc.

469 W. Parkland Drive

Sandy, UT 84070

www.desbio.com

800-827-8204

PACKAGE LABEL DISPLAY:

Des Bio

Upper Respiratory Support

Homeopathic

NDC 43742-1019-1

1 FL OZ (30 ml)